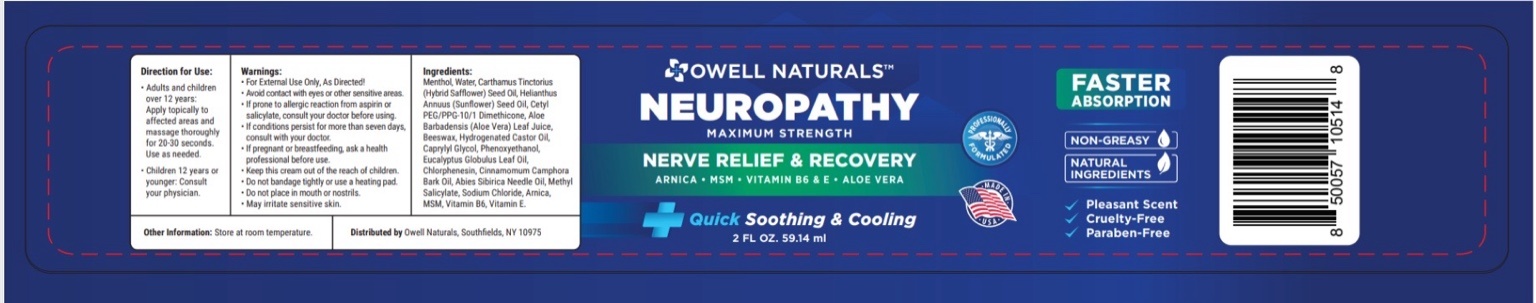 DRUG LABEL: Neuropathy Cream
NDC: 83570-001 | Form: CREAM
Manufacturer: Owell Naturals Brand, LLC
Category: otc | Type: HUMAN OTC DRUG LABEL
Date: 20260115

ACTIVE INGREDIENTS: MENTHOL 4 g/100 g

Active ingredient

Mentho1 4%

Purpose

Extenal Analgesic

Uses

Temporarily relieves minor aches and pains of muscles and joints.

Do not use

On wound or Damage skin

When using this product

do not get into eyes or mucous membranes
do not bandage tightly

Stop use and ask a doctor if

condition worsens
symptoms persist for more than 7 days or clear up and occur again within a few days

Keep out of reach of children

If swallowed, get medical help or contact a Poison Control Center right away.

Directions

adults and children 12 years of age and older:
apply to affected area no more than 3 to 4 times daily

children under 12 years of age:
ask a doctor

Questions?

Questions or comments?
Call 1-800-XXX-XXXX
Manufactured for: Your Company Name
City, State, ZIP

WARNINGS

For external use only.

Do not use on:
• Broken skin
• Wounds
• Irritated skin

When using this product:
• Avoid contact with eyes and mucous membranes
• Do not bandage tightly
• Do not apply heat to the treated area

Stop use and ask a doctor if:
• Condition worsens
• Symptoms persist for more than 7 days
• Redness or irritation develops

Keep out of reach of children.
If swallowed, get medical help or contact a Poison Control Center right away.

Inactive ingredients: purified water, glycerin

none

Principal Display Panel

Neuropathy Cream

Menthol 1%

Topical Analgesic

Net Wt. XX oz (XX g)

For external use only

Distributed by:
Owell Naturals Brand, LLC
USA

Principal Display Panel

See product label image.

principlal display panel

see product image